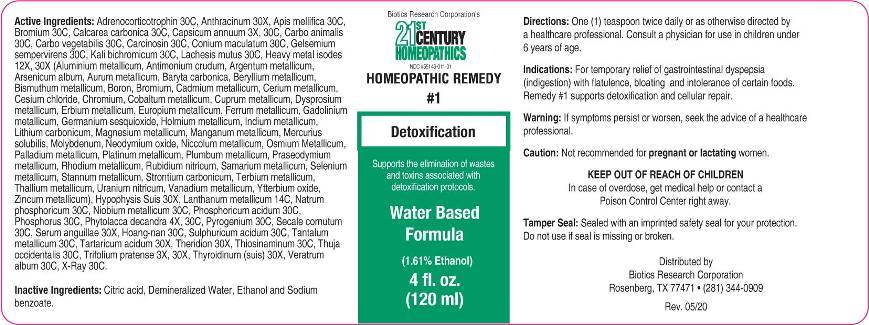 DRUG LABEL: 1 Detoxification
NDC: 55146-011 | Form: LIQUID
Manufacturer: Biotics Research Corporation
Category: otc | Type: HUMAN OTC DRUG LABEL
Date: 20200519

ACTIVE INGREDIENTS: TRIFOLIUM PRATENSE FLOWER 3 [hp_X]/1 mL; CAPSICUM 3 [hp_X]/1 mL; PHYTOLACCA AMERICANA ROOT 4 [hp_X]/1 mL; ALUMINUM 12 [hp_X]/1 mL; ANTIMONY TRISULFIDE 12 [hp_X]/1 mL; SILVER 12 [hp_X]/1 mL; ARSENIC TRIOXIDE 12 [hp_X]/1 mL; GOLD 12 [hp_X]/1 mL; BARIUM CARBONATE 12 [hp_X]/1 mL; BERYLLIUM 12 [hp_X]/1 mL; BISMUTH 12 [hp_X]/1 mL; BORON 12 [hp_X]/1 mL; BROMINE 12 [hp_X]/1 mL; CADMIUM 12 [hp_X]/1 mL; CERIUM 12 [hp_X]/1 mL; CESIUM CHLORIDE 12 [hp_X]/1 mL; CHROMIUM 12 [hp_X]/1 mL; COBALT 12 [hp_X]/1 mL; COPPER 12 [hp_X]/1 mL; DYSPROSIUM 12 [hp_X]/1 mL; ERBIUM 12 [hp_X]/1 mL; EUROPIUM 12 [hp_X]/1 mL; IRON 12 [hp_X]/1 mL; GADOLINIUM 12 [hp_X]/1 mL; GERMANIUM SESQUIOXIDE 12 [hp_X]/1 mL; HOLMIUM 12 [hp_X]/1 mL; INDIUM 12 [hp_X]/1 mL; LITHIUM CARBONATE 12 [hp_X]/1 mL; MAGNESIUM 12 [hp_X]/1 mL; MANGANESE 12 [hp_X]/1 mL; MERCURIUS SOLUBILIS 12 [hp_X]/1 mL; MOLYBDENUM 12 [hp_X]/1 mL; NEODYMIUM OXIDE 12 [hp_X]/1 mL; NICKEL 12 [hp_X]/1 mL; OSMIUM 12 [hp_X]/1 mL; PALLADIUM 12 [hp_X]/1 mL; PLATINUM 12 [hp_X]/1 mL; LEAD 12 [hp_X]/1 mL; PRASEODYMIUM 12 [hp_X]/1 mL; RHODIUM 12 [hp_X]/1 mL; RUBIDIUM NITRITE 12 [hp_X]/1 mL; SAMARIUM 12 [hp_X]/1 mL; SELENIUM 12 [hp_X]/1 mL; TIN 12 [hp_X]/1 mL; STRONTIUM CARBONATE 12 [hp_X]/1 mL; TERBIUM 12 [hp_X]/1 mL; THALLIUM 12 [hp_X]/1 mL; URANYL NITRATE HEXAHYDRATE 12 [hp_X]/1 mL; VANADIUM 12 [hp_X]/1 mL; YTTERBIUM OXIDE 12 [hp_X]/1 mL; ZINC 12 [hp_X]/1 mL; BACILLUS ANTHRACIS IMMUNOSERUM RABBIT 30 [hp_X]/1 mL; SUS SCROFA PITUITARY GLAND 30 [hp_X]/1 mL; ANGUILLA ROSTRATA BLOOD SERUM 30 [hp_X]/1 mL; TARTARIC ACID 30 [hp_X]/1 mL; THERIDION CURASSAVICUM 30 [hp_X]/1 mL; SUS SCROFA THYROID 30 [hp_X]/1 mL; LANTHANUM 14 [hp_C]/1 mL; CORTICOTROPIN 30 [hp_C]/1 mL; APIS MELLIFERA 30 [hp_C]/1 mL; OYSTER SHELL CALCIUM CARBONATE, CRUDE 30 [hp_C]/1 mL; CARBO ANIMALIS 30 [hp_C]/1 mL; ACTIVATED CHARCOAL 30 [hp_C]/1 mL; HUMAN BREAST TUMOR CELL 30 [hp_C]/1 mL; CONIUM MACULATUM FLOWERING TOP 30 [hp_C]/1 mL; GELSEMIUM SEMPERVIRENS ROOT 30 [hp_C]/1 mL; STRYCHNOS WALLICHIANA BARK 30 [hp_C]/1 mL; POTASSIUM DICHROMATE 30 [hp_C]/1 mL; LACHESIS MUTA VENOM 30 [hp_C]/1 mL; SODIUM PHOSPHATE, DIBASIC, HEPTAHYDRATE 30 [hp_C]/1 mL; NIOBIUM 30 [hp_C]/1 mL; PHOSPHORIC ACID 30 [hp_C]/1 mL; PHOSPHORUS 30 [hp_C]/1 mL; RANCID BEEF 30 [hp_C]/1 mL; CLAVICEPS PURPUREA SCLEROTIUM 30 [hp_C]/1 mL; SULFURIC ACID 30 [hp_C]/1 mL; TANTALUM 30 [hp_C]/1 mL; ALLYLTHIOUREA 30 [hp_C]/1 mL; THUJA OCCIDENTALIS LEAFY TWIG 30 [hp_C]/1 mL; VERATRUM ALBUM ROOT 30 [hp_C]/1 mL; ALCOHOL, X-RAY EXPOSED (1000 RAD) 30 [hp_C]/1 mL
INACTIVE INGREDIENTS: CITRIC ACID MONOHYDRATE; SODIUM BENZOATE; ALCOHOL; WATER

Drug Facts:

ACTIVE INGREDIENTS:

Trifolium Pratense 3X, 30X, Capsicum Annuum 3X, 30C, Phytolacca Decandra 4X, 30C, Aluminum Metallicum 12X, 30X, Antimonium Crudum 12X, 30X, Argentum Metallicum 12X, 30X, Arsenicum Album 12X, 30X, Aurum Metallicum 12X, 30X, Baryta Carbonica 12X, 30X, Beryllium Metallicum 12X, 30X, Bismuthum Metallicum 12X, 30X, Boron 12X, 30X, Bromium 12X, 30X, Cadmium Metallicum 12X, 30X, Cerium Metallicum 12X, 30X, Cesium Chloride 12X, 30X, Chromium 12X, 30X, Cobaltum Metallicum 12X, 30X, Cuprum Metallicum 12X, 30X, Dysprosium Metallicum 12X, 30X, Erbium Metallicum 12X, 30X, Europium Metallicum 12X, 30X, Ferrum Metallicum 12X, 30X, Gadolinium Metallicum 12X, 30X, Germanium Sesquioxide 12X, 30X, Holmium Metallicum 12X, 30X, Indium Metallicum 12X, 30X, Lithium Carbonicum 12X, 30X, Magnesium Metallicum 12X, 30X, Manganum Metallicum 12X, 30X, Mercurius Solubilis 12X, 30X, Molybdenum 12X, 30X, Neodymium Oxide 12X, 30X, Niccolum Metallicum 12X, 30X, Osmium Metallicum 12X, 30X, Palladium Metallicum 12X, 30X, Platinum Metallicum 12X, 30X, Plumbum Metallicum 12X, 30X, Praseodymium Metallicum 12X, 30X, Rhodium Metallicum 12X, 30X, Rubidium Nitricum 12X, 30X, Samarium Metallicum 12X, 30X, Selenium Metallicum 12X, 30X, Stannum Metallicum 12X, 30X, Strontium Carbonicum 12X, 30X, Terbium Metallicum 12X, 30X, Thallium Metallicum 12X, 30X, Uranium Nitricum 12X, 30X, Vanadium Metallicum 12X, 30X, Ytterbium Oxide 12X, 30X, Zincum Metallicum 12X, 30X, Anthracinum 30X, Hypophysis Suis 30X, Serum Anguillae 30X, Tartaricum Acidum 30X, Theridion 30X, Thyroidinum (Suis) 30X, Lanthanum Metallicum 14C, Adrenocorticotrophin 30C, Apis Mellifica 30C, Bromium 30C, Calcarea Carbonica 30C, Carbo Animalis 30C, Carbo Vegetabilis 30C, Carcinosin 30C, Conium Maculatum 30C, Gelsemium Sempervirens 30C, Hoang-Nan 30C, Kali Bichromicum 30C, Lachesis Mutus 30C, Natrum Phosphoricum 30C, Niobium Metallicum 30C, Phosphoricum Acidum 30C, Phosphorus 30C, Pyrogenium 30C, Secale Cornutum 30C, Sulphuricum Acidum 30C, Tantalum Metallicum 30C, Thiosinaminum 30C, Thuja Occidentalis 30C, Veratrum Album 30C, X-Ray 30C.

INDICATIONS:

For temporary relief of gastrointestinal dyspepsia (indigestion) with flatulence, bloating and intolerance of certain foods. Remedy #1 supports detoxification and cellular repair.

WARNINGS:

If symptoms persist or worsen, seek the advice of a healthcare professional.

Caution: Not recommended for pregnant or lactating women.

KEEP OUT OF REACH OF CHILDREN

In case of overdose, get medical help or contact a Poison Control Center right away.

Tamper Seal: Sealed with an imprinted safety seal for your protection. Do not use if seal is missing or broken.

KEEP OUT OF REACH OF CHILDREN:

In case of overdose, get medical help or contact a Poison Control Center right away.

DIRECTIONS:

One (1) teaspoon twice daily or as otherwise directed by a healthcare professional.

Consult a physician for use in children under 6 years of age.

INDICATIONS:

For temporary relief of gastrointestinal dyspepsia (indigestion) with flatulence, bloating and intolerance of certain foods. Remedy #1 supports detoxification and cellular repair.

INACTIVE INGREDIENTS:

Citric acid, Demineralized water, Ethanol and Sodium benzoate.

QUESTIONS:

Distributed by

Biotics Research Corporation

Rosenberg, TX 77471 • (281) 344-0909

PACKAGE LABEL DISPLAY:

Biotics Research Corporation's

21ST CENTURY
HOMEOPATHICS
NDC #55146-011-01

HOMEOPATHIC REMEDY
#1
Detoxification

Water Based

Formula

4 fl. oz.
(120 ml)